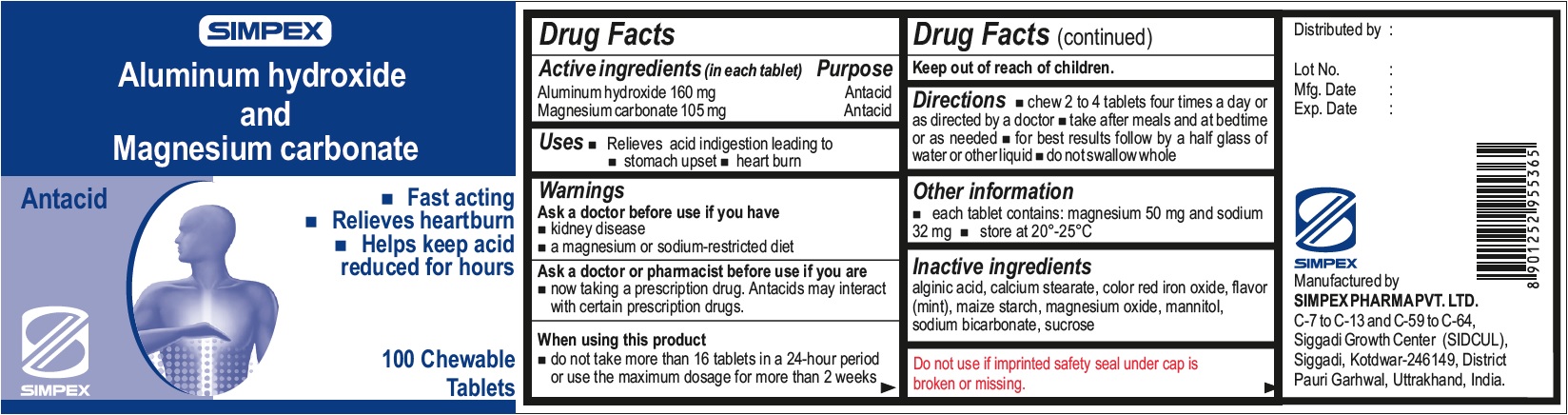 DRUG LABEL: Aluminum hydroxide and Magnesium carbonate

NDC: 76457-001 | Form: TABLET, CHEWABLE
Manufacturer: Simpex Pharma Pvt. Ltd
Category: otc | Type: HUMAN OTC DRUG LABEL
Date: 20231129

ACTIVE INGREDIENTS: ALUMINUM HYDROXIDE 160 mg/1 1; MAGNESIUM CARBONATE 105 mg/1 1
INACTIVE INGREDIENTS: ALGINIC ACID; CALCIUM STEARATE; FERRIC OXIDE RED; METHYL SALICYLATE; STARCH, CORN; MAGNESIUM OXIDE; MANNITOL; SODIUM BICARBONATE; SUCROSE

Aluminum hydroxide and Magnesium carbonate

Active ingredient (in each tablet)

Aluminum hydroxide, 160 mg

Magnesium carbonate, 105 mg

Purpose

Antacid

Uses

Relieves acid indigestion leading to

- stomach upset
- heart burn

Warnings

Ask a doctor before use if you have

- kidney disease
- a magnesium or sodium-restricted diet

Ask a doctor or pharmacist before use if you are

- now taking a prescription drug. Antacids may interact with certain prescription drugs.

When using this product

do not take more than 16 tablets in a 24-hour period or use the maximum dosage for more than 2 weeks

Directions

- chew 2 to 4 tablets four times a day or as directed by a doctor
- take after meals and at bedtime or as needed
- for best results follow by a half glass of water or other liquid
- do not swallow whole

Other information

- each tablet contains: magnesium 50 mg and sodium 32 mg
- store at 20°-25°C

Inactive ingredients

alginic acid, calcium stearate, color red iron oxide, flavor (mint), maize starch, magnesium oxide, mannitol, sodium bicarbonate, sucrose